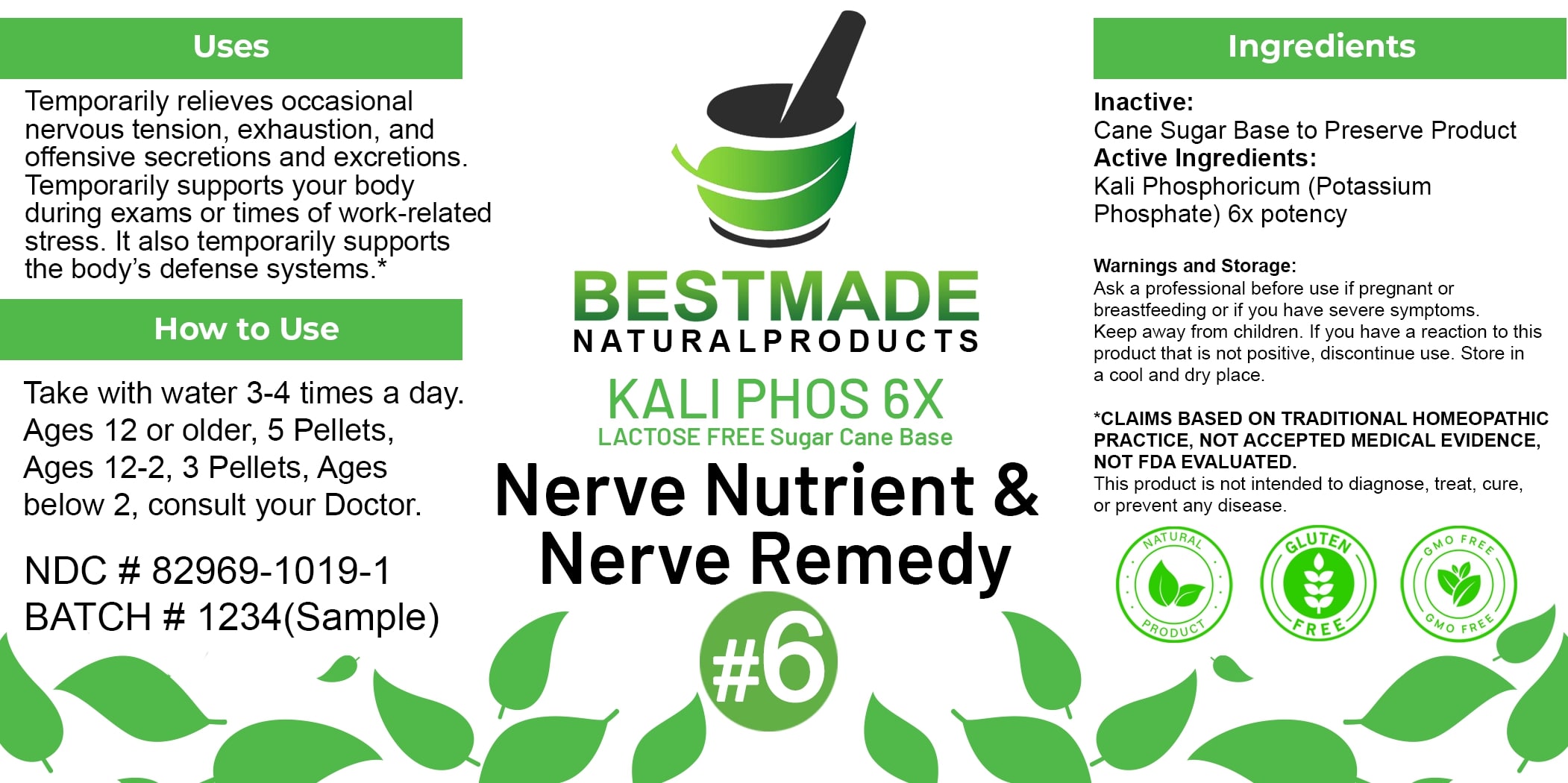 DRUG LABEL: Bestmade Natural Products Kali Phos (Lactose-Free)
NDC: 82969-1019 | Form: TABLET
Manufacturer: Bestmade Natural Products
Category: homeopathic | Type: HUMAN OTC DRUG LABEL
Date: 20250122

ACTIVE INGREDIENTS: POTASSIUM PHOSPHATE 6 [hp_X]/6 [hp_X]
INACTIVE INGREDIENTS: SUCROSE 6 [hp_X]/6 [hp_X]

Kali phos (lactose free)

DOSAGE AND ADMINISTRATION

How to Use

Take with water 3-4 times a day. Ages 12 or older, 5 Pellets, Ages 12-2, 3 Pellets, Ages below 2, consult your Doctor.

Uses

Temporarily relieves occasional nervous tension, exhaustion, and offensive secretions and excretions. Temporarily supports your body during exams or times of work-related stress. It also temporarily supports the body's defense systems.*

*CLAIMS BASED ON TRADITIONAL HOMEOPATHIC PRACTICE, NOT ACCEPTED MEDICAL EVIDENCE. NOT FDA EVALUATED. This product is not intended to diagnose, treat, cure, or prevent any disease.

INACTIVE INGREDIENT

Ingredients

Inactive: Cane Sugar Base to Preserve Product

Uses

Temporarily relieves occasional nervous tension, exhaustion, and offensive secretions and excretions. Temporarily supports your body during exams or times of work-related stress. It also temporarily supports the body's defense systems.*

*CLAIMS BASED ON TRADITIONAL HOMEOPATHIC PRACTICE, NOT ACCEPTED MEDICAL EVIDENCE. NOT FDA EVALUATED.

This product is not intended to diagnose, treat, cure, or prevent any disease.

Active Ingredients: Kali Phosphoricum (Potassium Phosphate) 6x potency

KEEP OUT OF REACH OF CHILDREN

Warnings and Storage:

Ask a professional before use if pregnant or breastfeeding or if you have severe symptoms. Keep away from children. If you have a reaction to this product that is not positive, discontinue use. Store in a cool and dry place.

Warnings and Storage:

Ask a professional before use if pregnant or breastfeeding or if you have severe symptoms. Keep away from children. If you have a reaction to this product that is not positive, discontinue use. Store in a cool and dry place.

*CLAIMS BASED ON TRADITIONAL HOMEOPATHIC PRACTICE, NOT ACCEPTED MEDICAL EVIDENCE. NOT FDA EVALUATED.

This product is not intended to diagnose, treat, cure, or prevent any disease.

Entire package label